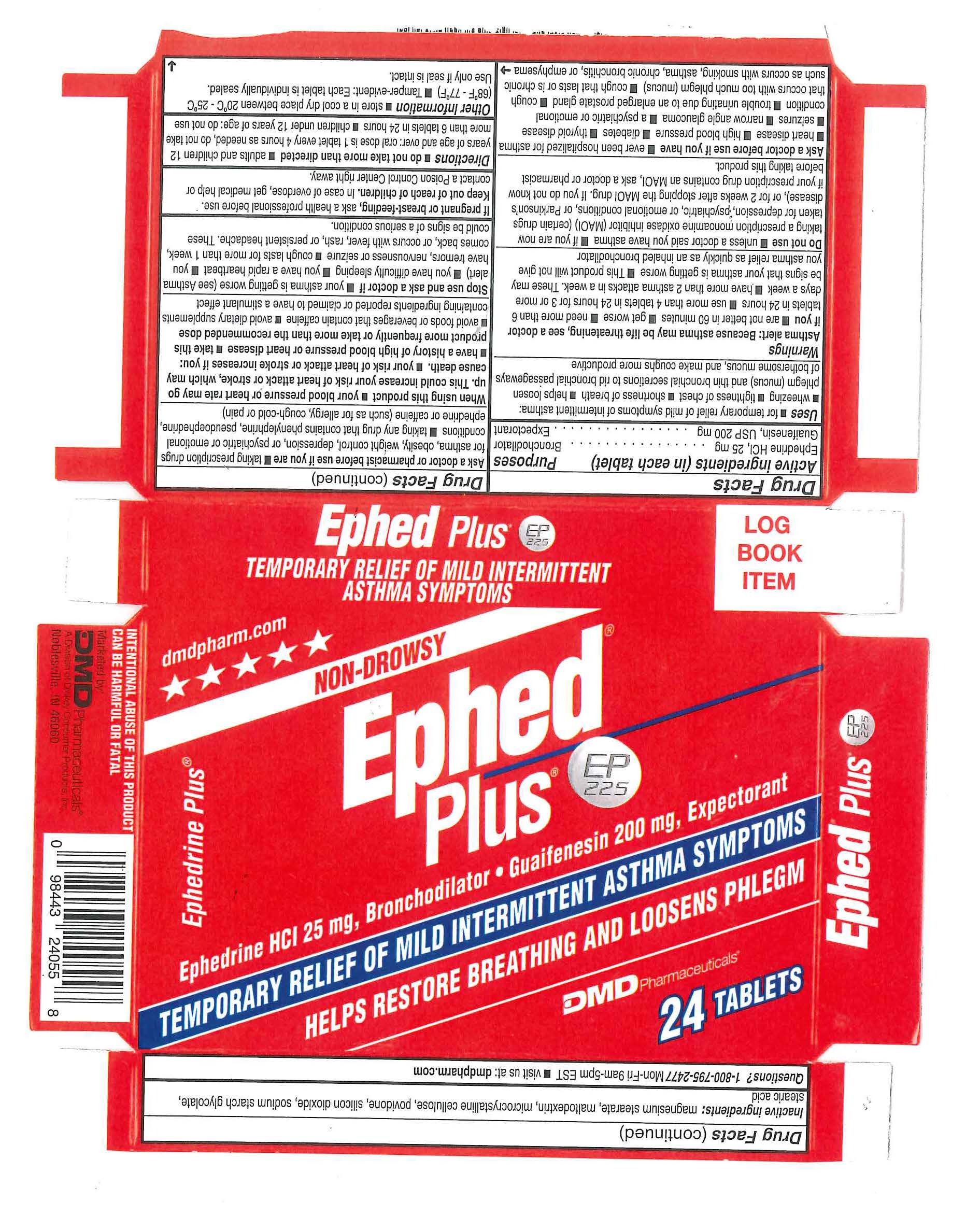 DRUG LABEL: Ephed Plus
NDC: 65193-225 | Form: TABLET
Manufacturer: Dickey Consumer Products DBA DMD
Category: otc | Type: HUMAN OTC DRUG LABEL
Date: 20190402

ACTIVE INGREDIENTS: EPHEDRINE HYDROCHLORIDE 25 mg/1 1; GUAIFENESIN 200 mg/1 1
INACTIVE INGREDIENTS: POVIDONE K30; STEARIC ACID; CELLULOSE, MICROCRYSTALLINE; SODIUM STARCH GLYCOLATE TYPE A POTATO; MALTODEXTRIN

DRUG FACTS

Active Ingredient(In Each Tablet): Ephedrine HCl 25 mg, Guaifenesin 200 mg

PURPOSE

Purposes - Bronchodilator, Expectorant

INDICATIONS AND USAGE

• for temporary relief of mild symptoms of intermittent asthma: • wheezing • tightness of chest • shortness of breath. Helps loosen phlegm (mucus) and thin bronchial secretions to rid bronchial passageways of bothersome mucus, and to make coughs more productive.

WARNINGS

Asthma Alert: because asthma may be life threatening, see a doctor if you: • Are not better in 60 minutes • get worse • need more than 6 tablets in 24 hours • use more than 4 tablets in 24 hours for 3 or more days a week • have more than 2 asthma attacks in a week. These may be signs that your asthma is getting worse. This product will not give you relief as quickly as an inhaled bronchodilator
Do not use: • Unless a doctor said you have asthma • if you are now taking a prescription monoamine oxidase inhibitor (MAOI) (Certain drugs for depression, psychiatric, or emotional conditions, or Parkinson's disease), or for 2 weeks after stopping the MAOI drug. If you do not know if your prescription drug contains an MAOI, ask a doctor or pharmacist before taking this product.
Ask a doctor before use if you have: • ever been hospitalized for asthma • heart disease • high blood pressure • diabetes • thyroid disease • seizures • narrow angle glaucoma • a psychiatric or emotional condition • trouble urinating due to an enlarged prostate gland • cough that occurs with too much phlegm (mucus) • cough that lasts or is chronic such as occurs with smoking, asthma, chronic bronchitis, or emphysema.
Ask a doctor or pharmacist before use if you are: • taking prescription drugs for asthma, obesity, weight control, depression, or psychiatric or emotional conditions. Taking any drug that contains phenylephrine, pseudoephedrine, ephedrine, or caffeine (such as for allergy, cough-cold, or pain)
When using this product • your blood pressure or heart rate may go up. This could increase your risk of heart attack or stroke, which may cause death. • your risk of heart attack or stroke increases if you:• have a history of high blood pressure or heart disease • take this product more frequently or take more than the recommended dose.
• avoid food or beverages that contain caffeine • Avoid dietary supplements containing ingredients reported or claim to have a stimulant effect.
Stop use and ask a doctor if: • your asthma is getting worse (see Asthma alert) • you have difficulty sleeping • you have a rapid heart beat • you have tremors, nervousness or seizures • cough lasts more than 1 week, comes back , or occurs with fever, rash, or persistent headache. These could be signs of a serious condition.

PREGNANCY OR BREAST FEEDING

If pregnant or breast feeding, ask a health proffessional before use

Keep out of reach of children. In case of overdose, get medical help or contact a Poison Control Center right away.

DOSAGE AND ADMINISTRATION

• do not take more than directed • adults and children 12 years of age and over: 1 tablet every 4 hours as needed, do not take more than 6 tablets in 24 hours • children under 12 years of age: do not use

INACTIVE INGREDIENT

Inactive Ingredients: Maltodextrin, Microcrystalline Cellulose, Povidone, Sodium Starch Glycolate,Stearic Acid